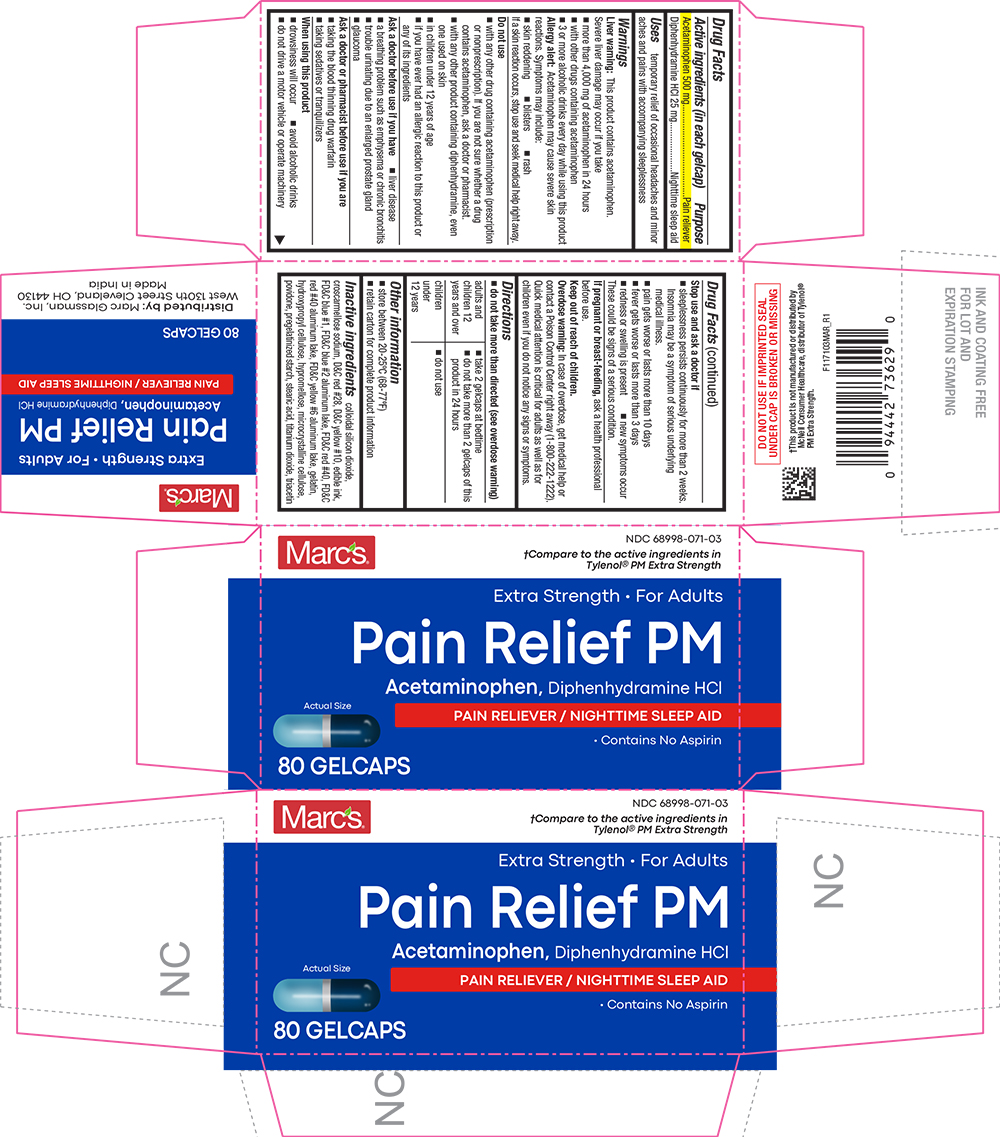 DRUG LABEL: Pain Relief PM
NDC: 68998-071 | Form: TABLET, COATED
Manufacturer: MARC GLASSMAN, INC.
Category: otc | Type: HUMAN OTC DRUG LABEL
Date: 20241023

ACTIVE INGREDIENTS: ACETAMINOPHEN 500 mg/1 1; DIPHENHYDRAMINE HYDROCHLORIDE 25 mg/1 1
INACTIVE INGREDIENTS: SILICON DIOXIDE; CROSCARMELLOSE SODIUM; D&C RED NO. 28; D&C YELLOW NO. 10; FD&C BLUE NO. 1; FD&C BLUE NO. 2; ALUMINUM OXIDE; FD&C RED NO. 40; FD&C YELLOW NO. 6; GELATIN; HYDROXYPROPYL CELLULOSE (1600000 WAMW); HYPROMELLOSES; CELLULOSE, MICROCRYSTALLINE; POVIDONE; STARCH, PREGELATINIZED CORN; STEARIC ACID; TITANIUM DIOXIDE; TRIACETIN

1171-MAR-2022-0915

Drug Facts

ACTIVE INGREDIENT

Active ingredients (in each gelcap) | Purpose
Acetaminophen 500 mg | Pain reliever
Diphenhydramine HCl 25 mg | Nighttime sleep-aid

Uses

temporary relief of occasional headaches and minor aches and pains with accompanying sleeplessness

Warnings

Liver warning

This product contains acetaminophen. Severe liver damage may occur if you take

- more than 4,000 mg of acetaminophen in 24 hours
- with other drugs containing acetaminophen
- 3 or more alcoholic drinks every day while using this product

Allergy alert

acetaminophen may cause severe skin reactions. Symptoms may include:

- skin reddening
- blisters
- rash

If a skin reaction occurs, stop use and seek medical help right away.

Do not use

- with any other drug containing acetaminophen (prescription or nonprescription). If you are not sure whether a drug contains acetaminophen, ask a doctor or pharmacist.
- with any other product containing diphenhydramine, even one used on skin
- in children under 12 years of age
- if you have ever had an allergic reaction to this product or any of its ingredients

Ask a doctor before use if you have

- liver disease
- a breathing problem such as emphysema or chronic bronchitis
- trouble urinating due to an enlarged prostate gland
- glaucoma

Ask a doctor or pharmacist before use if you are

- taking the blood thinning drug warfarin
- taking sedatives or tranquilizers

When using this product

- drowsiness will occur
- avoid alcoholic drinks
- do not drive a motor vehicle or operate machinery

Stop use and ask a doctor if

- sleeplessness persists continuously for more than 2 weeks. Insomnia may be a symptom of serious underlying medical illness.
- pain gets worse or lasts more than 10 days
- fever gets worse or lasts more than 3 days
- redness or swelling is present
- new symptoms occur

These could be signs of a serious condition

PREGNANCY OR BREAST FEEDING

If pregnant or breast-feeding, ask a health professional before use.

Keep out of reach of children.

Overdose warning

In case of overdose, get medical help or contact a Poison Control Center right away (1-800-222-1222). Quick medical attention is critical for adults as well as for children even if you do not notice any signs or symptoms.

Directions

- do not take more than directed (see overdose warning)

adults and children 12 years and over | - take 2 gelcaps at bedtime - do not take more than 2 gelcaps of this product in 24 hours
children under 12 years | - do not use

Other information

- store between 20-25ºC (68-77ºF)
- retain carton for complete product information

Inactive ingredients

colloidal silicon dioxide, croscarmellose sodium, D&C red #28, D&C yellow #10, edible ink, FD&C blue #1, FD&C blue #2 aluminum lake, FD&C red #40, FD&C red #40 aluminum lake, FD&C yellow #6 aluminum lake, gelatin, hydroxypropyl cellulose, hypromellose, microcrystalline cellulose, povidone, pregelatinized starch, stearic acid, titanium dioxide, triacetin

PRINCIPAL DISPLAY PANEL

Marc's®

NDC 68998-071-03

†Compare to the active ingredients in Tylenol® PM Extra Strength

Extra Strength • For Adults

Pain Relief PM

Acetaminophen, Diphenhydramine HCl

PAIN RELIEVER / NIGHTTIME SLEEP AID

• Contains No Aspirin

Actual size

80 GELCAPS